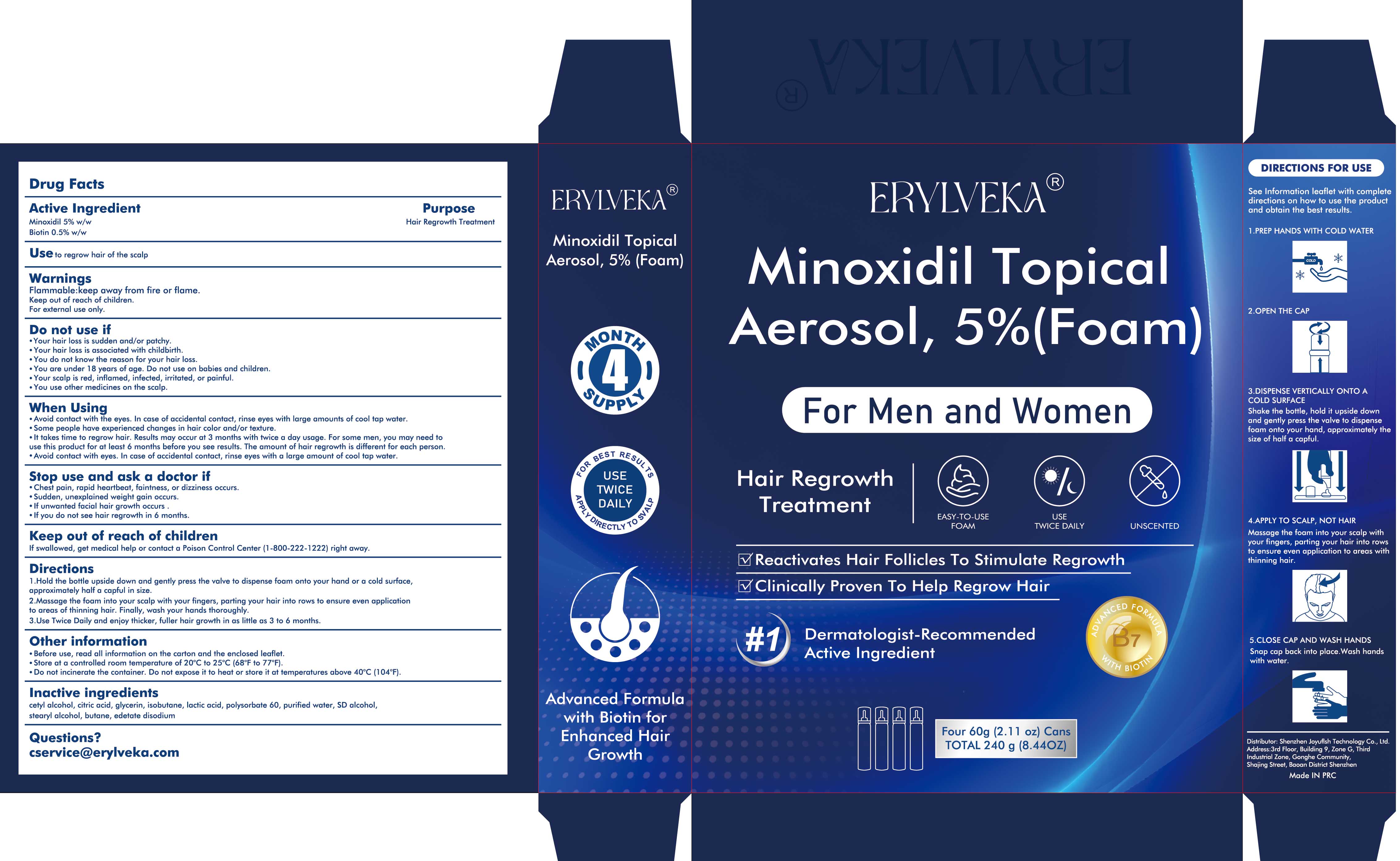 DRUG LABEL: ERYLVEKA 5% Minoxidil Hair Growth Foam with Biotin
NDC: 83766-104 | Form: AEROSOL, FOAM
Manufacturer: Shenzhen Joyuflsh Technology Co.,Ltd.
Category: otc | Type: HUMAN OTC DRUG LABEL
Date: 20250227

ACTIVE INGREDIENTS: MINOXIDIL 5 g/100 g; BIOTIN 0.5 g/100 g
INACTIVE INGREDIENTS: GLYCERIN; ISOBUTANE; POLYSORBATE 60; STEARYL ALCOHOL; EDETATE DISODIUM; CETYL ALCOHOL; BUTANE; LACTIC ACID; WATER; CITRIC ACID; ALCOHOL

ERYLVEKA 5% Minoxidil Hair Growth Foam with Biotin

ACTIVE INGREDIENT

Minoxidil 5%
Biotin 0.5%

PURPOSE

Hair Regrowth Treatment

INDICATIONS AND USAGE

Use to regrow hair of the scalp

WARNINGS

Flammable:keep away from fire or flame.
Keep out of reach of children.
For external use only,

DO NOT USE

.Your hair loss is sudden and/or patchy.
.Your hair loss is associated with childbirth.
.You do not know the reason for your hair loss.
.You are under 18 years of age. Do not use on babies and children.
.Your scalp is red, inflamed, infected, irritated, or painful.
.You use other medicines on the scalp.

WHEN USING

Avoid contact with the eyes. in case of accidental contact, rinse eyes with large amountsofcool tap water
Some people have experienced changes in hair color and/or texture.
lt takes time to regrow hair. Results may occur at 3 months with twice a day usage. For some men, you may need touse this product for at least 6 months before you see results. The amount of hair regrowth is different for each person
Avoid contact with eyes. in case of accidental contact, rinse eyes with a large amount of cool tap water.

STOP USE

Chest pain, rapid heartbeat, faintness, or dizziness occurs.
Sudden, unexplained weight gain occurs.
If unwanted facial hair growth occurs .
lf you do not see hair regrowth in 6 months.

KEEP OUT OF REACH OF CHILDREN

If swallowed, get medical help or contact a Poison Control Center (1-800-222-1222) right away.

DOSAGE AND ADMINISTRATION

1 .Hold the bottle upside down and gently press the valve to dispense foam onto your hand or a cold surfaceapproximately half a capful in size.
2.Massage the foam into your scalp with your fingers, parting your hair into rows to ensure even applicationto areas of thinning hair. Finally, wash your hands thoroughly.
3.Use Twice Daily and enjoy thicker, fuller hair growth in as little as 3 to 6 months.

STORAGE AND HANDLING

Before use, read all information on the carton and the enclosed leaflet
Store at a controlled room temperature of 20'C to 25°℃ (68°F to 77°F).
Do not incinerate the container. Do not expose it to heat or store it at temperatures above 40°C (104°F)

INACTIVE INGREDIENT

Biotin
cetyl alcohol
citric acid
glycerin
isobutane
lactic acid
polysorbate 60
purified water
SD alcohol
stearyl alcohol
butane
edetate disodium